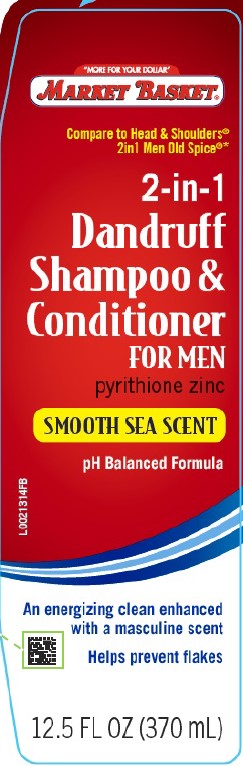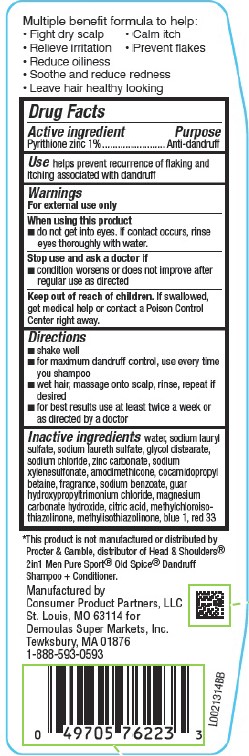 DRUG LABEL: Dandruff
NDC: 53942-253 | Form: SHAMPOO
Manufacturer: Demoulas Super Markets, Inc
Category: otc | Type: HUMAN OTC DRUG LABEL
Date: 20260203

ACTIVE INGREDIENTS: PYRITHIONE ZINC 10 mg/1 mL
INACTIVE INGREDIENTS: WATER; SODIUM LAURYL SULFATE; SODIUM LAURETH SULFATE; GLYCOL DISTEARATE; SODIUM CHLORIDE; ZINC CARBONATE; SODIUM XYLENESULFONATE; AMODIMETHICONE (800 CST); COCAMIDOPROPYL BETAINE; SODIUM BENZOATE; GUAR HYDROXYPROPYLTRIMONIUM CHLORIDE (1.7 SUBSTITUENTS PER SACCHARIDE); MAGNESIUM CARBONATE HYDROXIDE; CITRIC ACID MONOHYDRATE; METHYLCHLOROISOTHIAZOLINONE; METHYLISOTHIAZOLINONE; FD&C BLUE NO. 1; D&C RED NO. 33

Market Basket 253.001/253AB-AE
Men's Smooth Sea Scent Dandruff Shampoo and Conditioner

Claims

Multiple benefit formula to help:

- Fight dry scalp
- Calm itch
- Relieve irritation
- Prevent flakes
- Reduce oiliness
- Soothe and reduce redness
- Leave hair healthy looking

Active ingredient

Pyrithione zinc 1%

Purpose

Anti-dandruff

Use

helps prevent recurrence of flaking and itching associated with dandruff

Warnings

For external use only

When using this product

- do not get into eyes. If contact occurs, rinse eyes thoroughly with water.

Stop use and ask a doctor if

- condition worsens or does not improve after regular use as directed

Keep out of reach of children.

If swallowed, get medical help or contact a Poison Control Center right away.

Directions

- shake well
- for maximum dandruff control, use every time you shampoo
- wet hair, massage onto scalp, rinse, repeat if desired
- for best results use at least twice a week or as directed by a doctor

Inactive ingredients

water, sodium lauryl sulfate, sodium laureth sulfate, glycol distearate, sodium chloride, zinc carbonate, sodium xylenesulfonate, amodimethicone, cocamidopropyl betaine, fragrance, sodium benzoate, guar hydroxypropyltrimonium chloride, magnesium carbonate hydroxide, citric acid, methylchloroisothiazolinone, methylisothiazolinone, blue 1, red 33

Disclaimer

*This product is not manufactured or distributed by Procter & Gamble, distributor of Head & Shoulders® 2in1 Men Pure Sport® Old Spice® Dandruff Shampoo + Conditioner.

Adverse Reaction

Manufactured by Consumer Product Partners, LLC

St. Louis, MO 63114 for

Demoulas Super Markets, Inc.

Tewksbury, MA 01876

1-888-593-0593

Principal display panel

"MORE FOR YOUR DOLLAR"

MARKET BASKET®

Compare to Head & Shoulders®2in1 Men Old Spice®*

2-in-1

Dandruff

Shampoo &

Conditioner

FOR MEN

pyrithione zinc

SMOOTH SEA SCENT

pH Balanced Formula

An energizing clean enhanced with a masculine scent

Helps prevent flakes

12.5 FL OZ (370 mL)